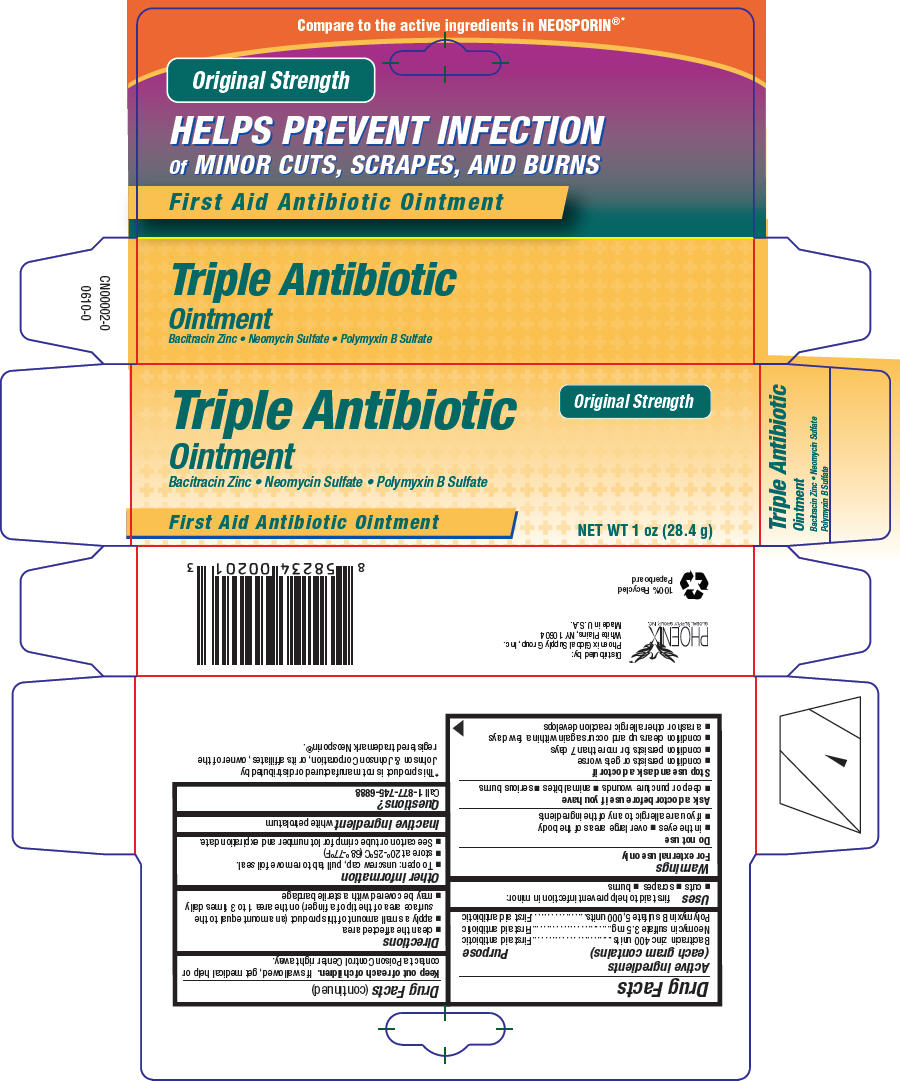 DRUG LABEL: Triple Antibiotic
NDC: 52426-020 | Form: OINTMENT
Manufacturer: Phoenix Global Supply Group, Inc
Category: otc | Type: HUMAN OTC DRUG LABEL
Date: 20100928

ACTIVE INGREDIENTS: Bacitracin zinc 400 [iU]/1 g; Neomycin sulfate 3.5 mg/1 g; Polymyxin B sulfate 5000 [iU]/1 g
INACTIVE INGREDIENTS: petrolatum

Triple Antibiotic
Ointment

Drug Facts

ACTIVE INGREDIENT

Active ingredients (each gram contains) | Purpose
Bacitracin zinc 400 units | First aid antibiotic
Neomycin sulfate 3.5 mg | First aid antibiotic
Polymyxin B sulfate 5,000 units | First aid antibiotic

Uses

first aid to help prevent infection in minor:

- cuts
- scrapes
- burns

Warnings

For external use only

Do not use

- in the eyes
- over large areas of the body
- if you are allergic to any of the ingredients

Ask a doctor before use if you have

- deep or puncture wounds
- animal bites
- serious burns

Stop use and ask a doctor if

- condition persists or gets worse
- condition persists for more than 7 days
- condition clears up and occurs again within a few days
- a rash or other allergic reaction develops

Keep out of reach of children. If swallowed, get medical help or contact a Poison Control Center right away.

Directions

- clean the affected area
- apply a small amount of this product (an amount equal to the surface area of the tip of a finger) on the area 1 to 3 times daily
- may be covered with a sterile bandage

Other information

- To open: unscrew cap, pull tab to remove foil seal.
- store at 20°-25°C (68°-77°F)
- See carton or tube crimp for lot number and expiration date.

Inactive ingredient

white petrolatum

Questions?

Call 1-877-745-6888

Distributed by:
Phoenix Global Supply Group, Inc.
White Plains, NY 10604

PRINCIPAL DISPLAY PANEL - 28.4 g Tube Carton

Triple Antibiotic
Ointment
Bacitracin Zinc • Neomycin Sulfate • Polymyxin B Sulfate

First Aid Antibiotic Ointment

Original Strength

NET WT 1 oz (28.4 g)